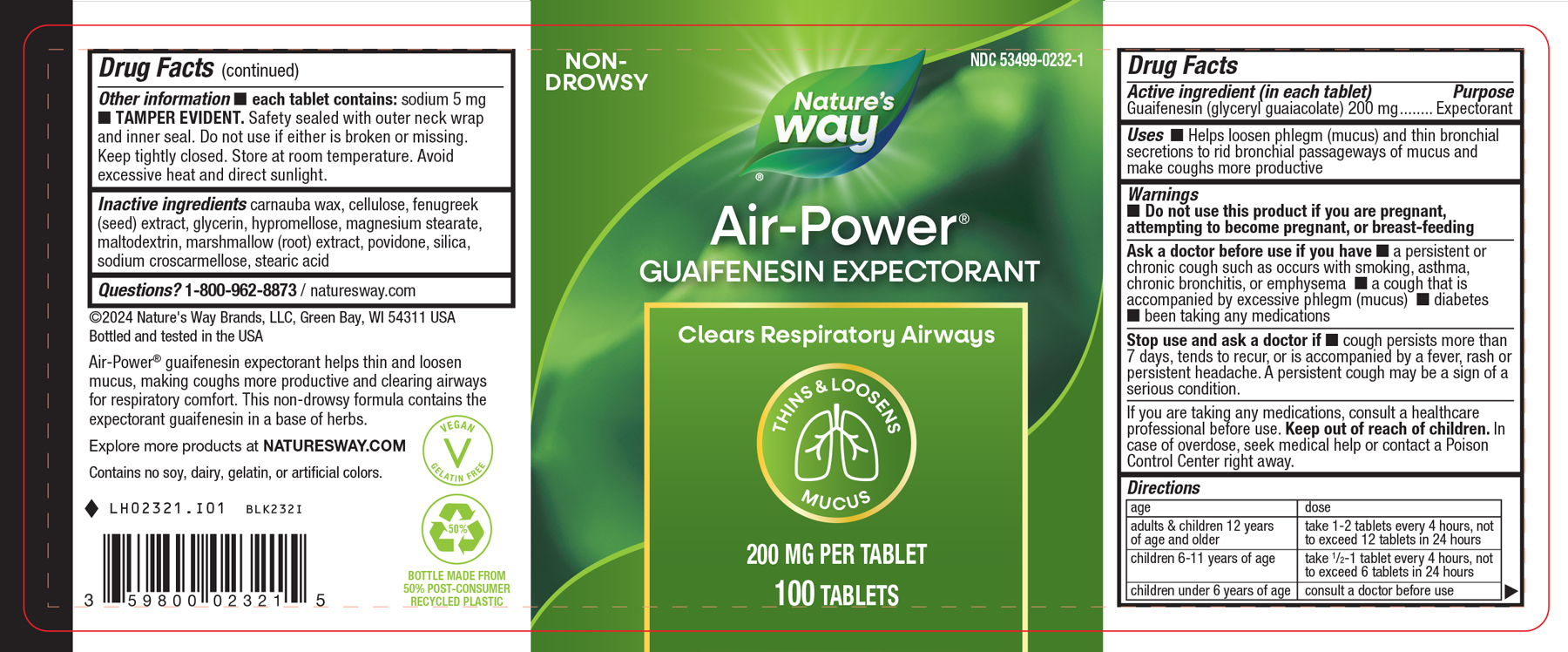 DRUG LABEL: Air Power
								
NDC: 53499-0232 | Form: TABLET
Manufacturer: Schwabe North America, Inc
Category: otc | Type: HUMAN OTC DRUG LABEL
Date: 20251002

ACTIVE INGREDIENTS: GUAIFENESIN 200 mg/1 1
INACTIVE INGREDIENTS: CARNAUBA WAX; MICROCRYSTALLINE CELLULOSE; FENUGREEK SEED; GLYCERIN; HYPROMELLOSE, UNSPECIFIED; MAGNESIUM STEARATE; MALTODEXTRIN; ALTHAEA OFFICINALIS ROOT; POVIDONE; SILICON DIOXIDE; CROSCARMELLOSE SODIUM; STEARIC ACID

AIR POWER

Active Ingredient:

Guaifenesin 200 mg

Inactive Ingredients:

Carnauba Wax

Cellulose

Fenugreek (seed) Extract

Glycerin

Hypromellose

Magnesium Stearate

Maltodextrin

Marshmallow (root) Extract

Povidone

Silica

Sodium Croscarmellose

Stearic Acid

Dosage & Administration:

Adults & children 12 years and older: take 1-2 tablets every 4 hours, not to exceed 12 tablets in 24 hours

Children 6 to 11 years of age: take ½ to 1 tablet every 4 hours, not to exceed 6 tablets in 24 hours

Children under 6 years of age: consult a doctor before use

Purpose:

Helps loosen phlegm (mucus) and thin bronchial secretions to rid bronchial passageways of mucus and make coughs more productive.

Indications & Useage:

Helps loosen phlegm (mucus) and thin bronchial secretions to rid bronchial passageways of mucus and make coughs more productive.

Warnings:

Do not use this product if you are pregnant, attempting to become pregnant, or breast-feeding.

Ask a doctor before use if you have a persistent or chronic cough such as occurs with smoking, asthma, chronic bronchitis, or emphysema, a cough that is accompanied by excessive phlegm (mucus), diabetes, been taking any medications.

Stop Use:

Stop use and ask a doctor if cough persists more than 7 days, tends to recur, or is accompanied by a fever, rash or persisient headache.

A persistent cough may be a sign of a serious condition.

If you are taking any medications, consult a healthcare professional before use.

Keep out of Reach of Children:

Overdosage:

In case of overdose, seek medical help or contact a Poison Control Center right away.